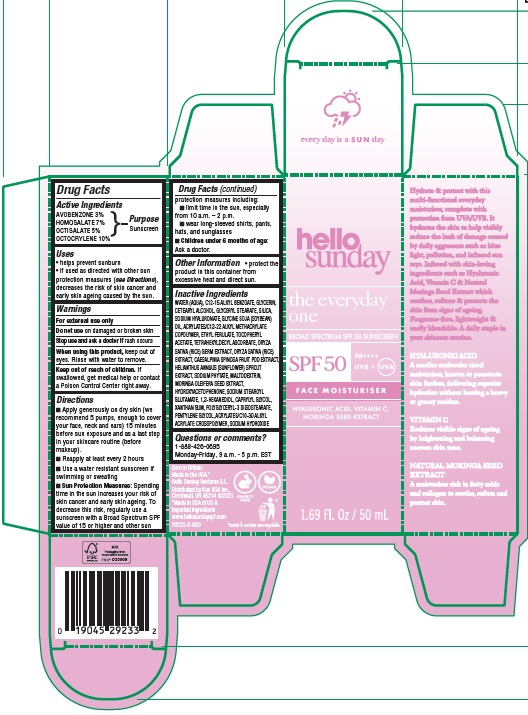 DRUG LABEL: Hello Sunday The Everyday One Face Moisturiser SPF 50
NDC: 10596-802 | Form: EMULSION
Manufacturer: Kao USA Inc.
Category: otc | Type: HUMAN OTC DRUG LABEL
Date: 20241112

ACTIVE INGREDIENTS: OCTISALATE 50 mg/1 mL; OCTOCRYLENE 100 mg/1 mL; HOMOSALATE 70 mg/1 mL; AVOBENZONE 30 mg/1 mL
INACTIVE INGREDIENTS: MALTODEXTRIN; MORINGA OLEIFERA SEED; WATER; HYALURONATE SODIUM; RICE GERM; GLYCERIN; ETHYL FERULATE; TETRAHEXYLDECYL ASCORBATE; CAESALPINIA SPINOSA FRUIT POD; HELIANTHUS ANNUUS SPROUT; PHYTATE SODIUM; HYDROXYACETOPHENONE; SODIUM STEAROYL GLUTAMATE; 1,2-HEXANEDIOL; ALKYL (C12-15) BENZOATE; XANTHAN GUM; ALPHA-TOCOPHEROL ACETATE; ACRYLATES/C10-30 ALKYL ACRYLATE CROSSPOLYMER (60000 MPA.S); CAPRYLYL GLYCOL; PENTYLENE GLYCOL; POLYGLYCERYL-3 DIISOSTEARATE; SODIUM HYDROXIDE; SOYBEAN OIL; GLYCERYL MONOSTEARATE; SILICON DIOXIDE; CETOSTEARYL ALCOHOL

Hello Sunday The Everyday One Face Moisturiser SPF 50

Active Ingredients

AVOBENZONE 3%
HOMOSALATE 7%
OCTISALATE 5%
OCTOCRYLENE 10%

Purpose

Sunscreen

Uses

- helps prevent sunburn
- if used as directed with other sun protection measures (see Directions), decreases the risk of skin cancer and early skin ageing caused by the sun.

Warnings

For external use only

Do not use

on damaged or broken skin

Stop use and ask a doctor if

rash occurs

When using this product

keep out of eyes. Rinse with water to remove.

Keep out of reach of children.

If swallowed, get medical help or contact a Poison Control Center right away.

Directions

- Apply generously on dry skin (we recommend 5 pumps, enough to cover your face, neck and ears), 15 minutes before sun exposure and as a last step in your skincare routine (before makeup).
- Reapply at least every 2 hours.
- Use a water resistant sunscreen if swimming or sweating
- Sun Protection Measures: Spending time in the sun increases your risk of skin cancer and early skin ageing. To decrease this risk, regularly use a sunscreen with a Broad Spectrum SPF value of 15 or higher and other sun protection measures including:
- limit time in the sun, especially from 10 a.m. – 2 p.m.
- wear long-sleeved shirts, pants, hats, and sunglasses
- Children under 6 months of age: Ask a doctor.

Other Information

- protect the product in this container from excessive heat and direct sun.

Inactive Ingredients

WATER (AQUA), C12-15 ALKYL BENZOATE, GLYCERIN, CETEARYL ALCOHOL, GLYCERYL STEARATE, SILICA, SODIUM HYALURONATE, GLYCINE SOJA (SOYBEAN) OIL, ACRYLATES/C12-22 ALKYL METHACRYLATE COPOLYMER, ETHYL FERULATE, TOCOPHERYL ACETATE, TETRAHEXYLDECYL ASCORBATE, ORYZA SATIVA (RICE) GERM EXTRACT, ORYZA SATIVA (RICE) EXTRACT, CAESALPINIA SPINOSA FRUIT POD EXTRACT, HELIANTHUS ANNUUS (SUNFLOWER) SPROUT EXTRACT, SODIUM PHYTATE, MALTODEXTRIN, MORINGA OLEIFERA SEED EXTRACT, HYDROXYACETOPHENONE, SODIUM STEAROYL GLUTAMATE, 1,2-HEXANEDIOL, CAPRYLYL GLYCOL, XANTHAN GUM, POLYGLYCERYL-3 DIISOSTEARATE, PENTYLENE GLYCOL, ACRYLATES/C10-30 ALKYL ACRYLATE CROSSPOLYMER, SODIUM HYDROXIDE

Questions or comments?

1-888-426-0695
Monday-Friday, 9 a.m. - 5 p.m. EST